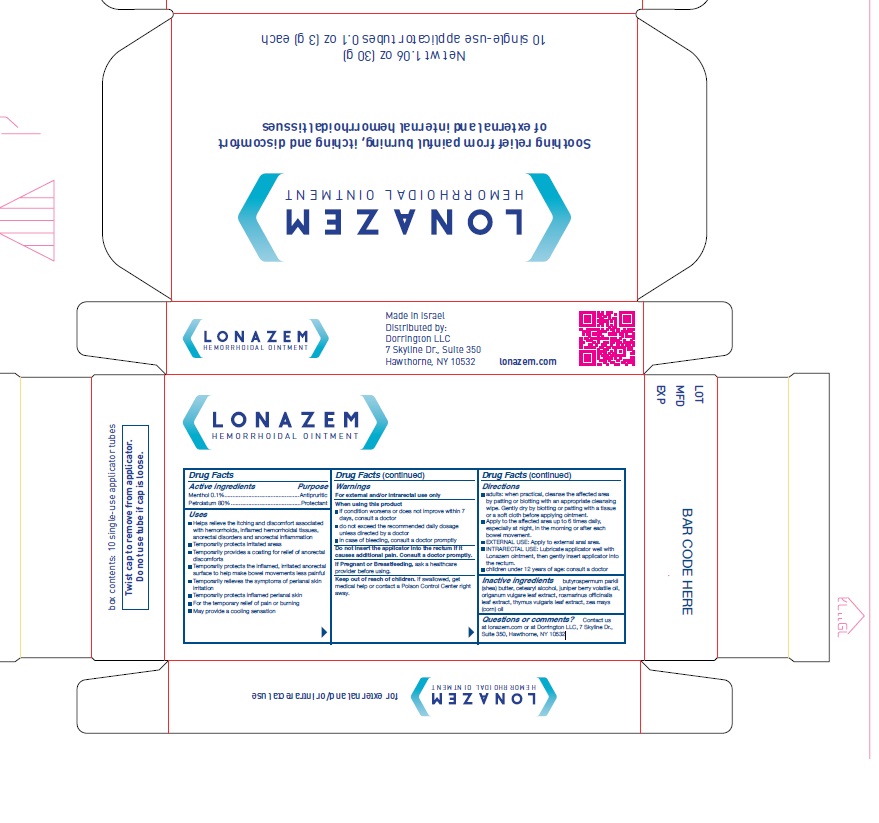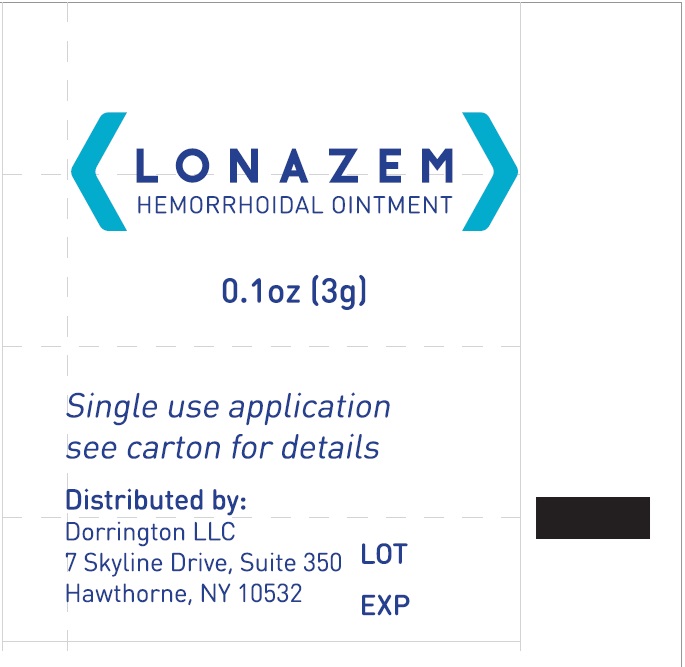 DRUG LABEL: LONAZEM
NDC: 69435-1200 | Form: OINTMENT
Manufacturer: PEER PHARM LTD.
Category: otc | Type: HUMAN OTC DRUG LABEL
Date: 20260112

ACTIVE INGREDIENTS: MENTHOL 0.1 g/100 g; PETROLATUM 80 g/100 g
INACTIVE INGREDIENTS: JUNIPER BERRY OIL; OREGANO; THYMUS VULGARIS LEAF; ROSEMARY; CORN OIL; SHEA BUTTER; CETOSTEARYL ALCOHOL

Active Ingredients

Menthol 0.1%
Petrolatum 80%

Purpose

Menthol…….Antipruritic
Petrolatum…..Protectant

Uses

- Helps relieve the itching and discomfort associated with hemorrhoids, inflamed hemorrhoidal tissues, anorectal disorders and anorectal inflammation
- Temporarily protects irritated areas
- Temporarily provides a coating for relief of anorectal discomforts
- Temporarily protects the inflamed, irritated anorectal surface to help make bowel movements less painful
- Temporarily relieves the symptoms of perianal skin irritation
- Temporarily protects inflamed perianal skin
- For the temporary relief of pain or burning
- May provide a cooling sensation

Warnings

- For external and/or intrarectal use only
- When using this product

if condition worsens or does not improve within 7 days, consult a doctor

do not exceed the recommended daily dosage unless directed by a doctor

in case of bleeding, consult a doctor promptly

- Do not insert the applicator into the rectum if it causes additional pain. Consult a doctor promptly.

If Pregnant or Breastfeeding, ask a healthcare provider before using.

Keep out of reach of children. If swallowed, get medical help or contact a Poison Control Center right away.

Directions

- adults: when practical, cleanse the affected area by patting or blotting with an appropriate cleansing wipe. Gently dry by blotting or patting with a tissue or a soft cloth before applying ointment.
- Apply to the affected area up to 6 times daily, especially at night, in the morning or after ' each bowel movement.
- EXTERNAL USE: Apply to external anal area.
- INTRARECTAL USE: Lubricate applicator well with Lonazem ointment, then gently insert applicator into the rectum.
- Children under 12 years of age: consult a doctor

Inactive Ingredients

butyrospermum parkii (shea) butter, cetearyl alcohol, juniper berry volatile oil, origanum vulgare leaf extract, rosmarinus officinalis leaf extract, thymus vulgaris leaf extract, zea mays (corn) oil

Questions or comments?

Contact us at lonazem.com or at Dorrington LLC, 7 Skyline Dr., Suite 350, Hawthorne, NY 10532